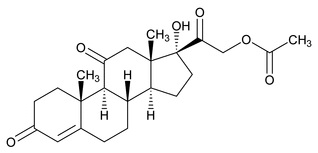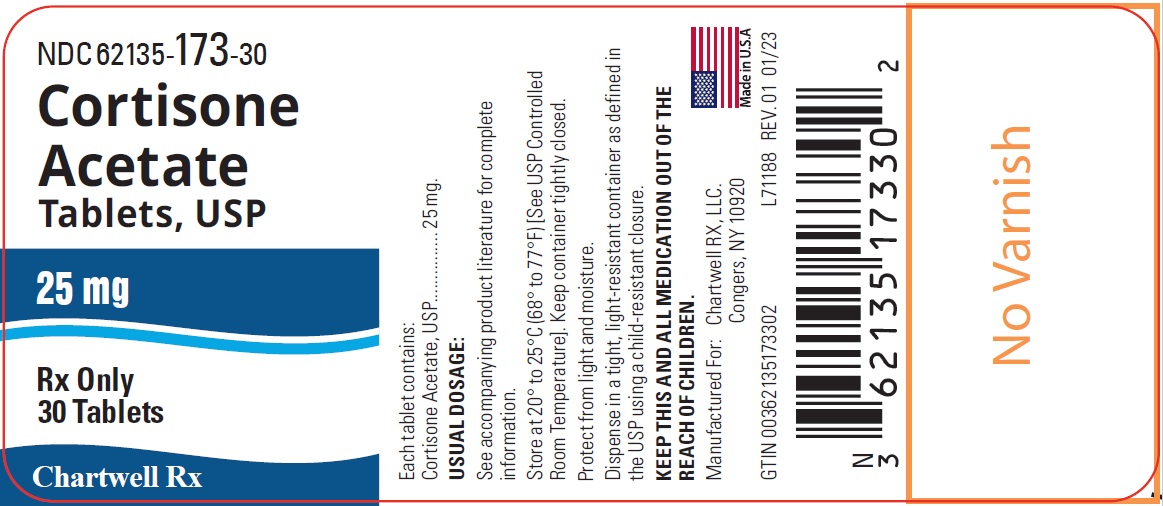 DRUG LABEL: Cortisone Acetate
NDC: 62135-173 | Form: TABLET
Manufacturer: Chartwell RX, LLC
Category: prescription | Type: HUMAN PRESCRIPTION DRUG LABEL
Date: 20250606

ACTIVE INGREDIENTS: CORTISONE ACETATE 25 mg/1 1
INACTIVE INGREDIENTS: STARCH, CORN; SUCROSE; LACTOSE MONOHYDRATE; CALCIUM STEARATE

CORTISONE ACETATE TABLETS, USP
Rx Only

DESCRIPTION:

Glucocorticoids are adrenocortical steroids, both naturally occurring and synthetic, which are readily absorbed from the gastrointestinal tract.

Cortisone acetate is a white or practically white, odorless, crystalline powder. It is stable in air. It is insoluble in water. The molecular weight is 402.48. It is designated chemically as 17,21-Dihydroxypregn-4-ene-3,11,20-trione 21-acetate. The molecular formula is C23H30O6 and the structural formula is:

Each tablet, for oral administration, contains 25 mg of cortisone acetate.

Inactive ingredients are lactose monohydrate, corn starch, sucrose, and calcium stearate.

CLINICAL PHARMACOLOGY:

Naturally occurring glucocorticoids (hydrocortisone and cortisone), which also have salt-retaining properties, are used as replacement therapy in adrenocortical deficiency states. They are also used for their potent anti-inflammatory effects in disorders of many organ systems.

Glucocorticoids cause profound and varied metabolic effects. In addition, they modify the body’s immune responses to diverse stimuli.

INDICATIONS AND USAGE:

When oral therapy is not feasible:

1. Endocrine Disorders

- Primary or secondary adrenocortical insufficiency (hydrocortisone or cortisone is the first choice; synthetic analogs may be used in conjunction with mineralocorticoids where applicable; in infancy mineralocorticoid supplementation is of particular importance).
- Congenital adrenal hyperplasia
- Nonsuppurative thyroiditis
- Hypercalcemia associated with cancer

2. Rheumatic Disorders

As adjunctive therapy for short-term administration (to tide the patient over an acute episode or exacerbation) in:

- Psoriatic arthritis
- Rheumatoid arthritis, including juvenile rheumatoid arthritis (selected cases may require low-dose maintenance therapy)
- Ankylosing spondylitis
- Acute and subacute bursitis
- Acute nonspecific tenosynovitis
- Acute gouty arthritis
- Post-traumatic osteoarthritis
- Synovitis of osteoarthritis
- Epicondylitis

3. Collagen Diseases

During an exacerbation or as maintenance therapy in selected cases of:

- Systemic lupus erythematosus
- Acute rheumatic carditis
- Systemic dermatomyositis (polymyositis)

4. Dermatologic Diseases

- Pemphigus
- Bullous dermatitis herpetiformis
- Severe erythema multiforme (Stevens-Johnson syndrome)
- Exfoliative dermatitis
- Mycosis fungoides
- Severe psoriasis
- Severe seborrheic dermatitis

5. Allergic States

Control of severe or incapacitating allergic conditions intractable to adequate trials of conventional treatment in:

- Seasonal or perennial allergic rhinitis
- Bronchial asthma
- Contact dermatitis
- Atopic dermatitis
- Serum sickness
- Drug hypersensitivity reactions

6. Ophthalmic Diseases
Severe acute and chronic allergic and inflammatory processes involving the eye and its adnexa, such as:

- Allergic conjunctivitis
- Keratitis
- Allergic corneal marginal ulcers
- Herpes zoster ophthalmicus
- Iritis and iridocyclitis
- Chorioretinitis
- Anterior segment inflammation
- Diffuse posterior uveitis and choroiditis
- Optic neuritis
- Sympathetic ophthalmia

7. Respiratory Diseases

- Symptomatic sarcoidosis
- Loeffler’s syndrome not manageable by other means
- Berylliosis
- Fulminating or disseminated pulmonary tuberculosis when used concurrently with appropriate antituberculosis chemotherapy
- Aspiration pneumonitis

8. Hematologic Disorders

- Idiopathic thrombocytopenic purpura in adults
- Secondary thrombocytopenia in adults
- Acquired (autoimmune) hemolytic anemia
- Erythroblastopenia (RBC anemia)
- Congenital (erythroid) hypoplastic anemia

9. Neoplastic Diseases

For palliative management of:

- Leukemias and lymphomas in adults
- Acute leukemia of childhood

10. Edematous States

- To induce a diuresis or remission of proteinuria in the nephrotic syndrome, without uremia, of the idiopathic type or that due to lupus erythematosus

11. Gastrointestinal Diseases

To tide the patient over a critical period of the disease in:

- Ulcerative colitis
- Regional enteritis

12. Miscellaneous

- Tuberculous meningitis with subarachnoid block or impending block when used concurrently with appropriate antituberculous chemotherapy
- Trichinosis with neurologic or myocardial involvement

CONTRAINDICATIONS:

• Systemic fungal infections
• Hypersensitivity to this product

WARNINGS:

In patients on corticosteroid therapy subjected to unusual stress, increased dosage of rapidly acting corticosteroids before, during, and after the stressful situation is indicated.

Immunosuppression and Increased Risk of Infection

Corticosteroids, including cortisone acetate tablets, suppress the immune system and increase the risk of infection with any pathogen, including viral, bacterial, fungal, protozoan, or helminthic pathogens. Corticosteroids can;

- Reduce resistance to new infections
- Exacerbate existing infections
- Increase the risk of disseminated infections
- Increase the risk of reactivation or exacerbation of latent infections
- Mask some signs of infection

Corticosteroid-associated infections can be mild but can be severe and at times fatal. The rate of infectious complication increases with increasing corticosteroid dosages.

Monitor for the development of infection and consider cortisone acetate tablets withdrawal or dosage reduction as needed.

Tuberculosis

If cortisone acetate tablets are used to treat a condition in patients with latent tuberculosis or tuberculin reactivity, reactivation of tuberculosis may occur. Closely monitor such patients for reactivation. During prolonged cortisone acetate therapy, patients with latent tuberculosis or tuberculin reactivity should receive chemoprophylaxis.

Varicella Zoster and Measles Viral Infections

Varicella and measles can have a serious or even fatal course in non-immune patients taking corticosteroids, including cortisone acetate tablets. In corticosteroid-treated patients who have not had these diseases or are nonimmune, particular care should be taken to avoid exposure to varicella and measles:

- If a cortisone acetate tablets-treated patient is exposed to varicella, prophylaxis with varicella zoster immune globulin may be indicated. If varicella develops, treatment with antiviral agents may be considered.
- If a cortisone acetate tablets-treated patient is exposed to measles, prophylaxis with immunoglobulin may be indicated.

Hepatitis B Virus Reactivation

Hepatitis B virus reactivation can occur in patients who are hepatitis B carriers treated with immunosuppressive dosages of corticosteroids, including cortisone acetate tablets. Reactivation can also occur infrequently in corticosteroid-treated patients who appear to have resolved hepatitis B infection.

Screen patients for hepatitis B infection before initiating immunosuppressive (e.g., prolonged) treatment with cortisone acetate tablets. For patients who show evidence of hepatitis B infection, recommend consultation with physicians with expertise in managing hepatitis B regarding monitoring and consideration for hepatitis B antiviral therapy.

Fungal Infections

Corticosteroids, including cortisone acetate tablets, may exacerbate systemic fungal infections; therefore, avoid cortisone acetate tablets use in the presence of such infections unless cortisone acetate tablets are needed to control drug reactions. For patients on chronic cortisone acetate tablets therapy who develop systemic fungal infections, cortisone acetate tablets withdrawal or dosage reduction is recommended.

Amebiasis

Corticosteroids, including cortisone acetate tablets, may activate latent amebiasis. Therefore, it is recommended that latent amebiasis or active amebiasis be ruled out before initiating cortisone acetate tablets in patients who have spent time in the tropics or patients with unexplained diarrhea.

Strongyloides Infestation

Corticosteroids, including cortisone acetate tablets, should be used with great care in patients with known or suspected Strongyloides (threadworm) infestation. In such patients, corticosteroid-induced immunosuppression may lead to Strongyloides hyperinfection and dissemination with widespread larval migration, often accompanied by severe enterocolitis and potentially fatal gram-negative septicemia.

Cerebral Malaria

Avoid corticosteroids, including cortisone acetate tablets, in patients with cerebral malaria.

Kaposi’s Sarcoma

Kaposi’s sarcoma has been reported to occur in patients receiving corticosteroid therapy, most often for chronic conditions. Discontinuation of corticosteroids may result in clinical improvement of Kaposi’s sarcoma.

Drug-induced secondary adrenocortical insufficiency may result from too rapid withdrawal of corticosteroids and may be minimized by gradual reduction of dosage. This type of relative insufficiency may persist for months after discontinuation of therapy; therefore, in any situation of stress occurring during that period, hormone therapy should be reinstituted. If the patient is receiving steroids already, dosage may have to be increased. Since mineralocorticoid secretion may be impaired, salt and/or a mineralocorticoid should be administered concurrently.

In cerebral malaria, a double-blind trial has shown that the use of corticosteroids is associated with prolongation of coma and a higher incidence of pneumonia and gastrointestinal bleeding.

Prolonged use of corticosteroids may produce posterior subsapsular cataracts, glaucoma with possible damage to the optic nerves, and may enhance the establishment of secondary ocular infections due to fungi or viruses.

Average and large doses of hydrocortisone or cortisone can cause elevation of blood pressure, salt and water retention, and increased excretion of potassium. These effects are less likely to occur with the synthetic derivatives except when used in large doses. Dietary salt restriction and potassium supplementation may be necessary. All corticosteroids increase calcium excretion.

Administration of live virus vaccines, including smallpox, is contraindicated in individuals receiving immunosuppressive doses of corticosteroids. If inactivated viral or bacterial vaccines are administered to individuals receiving immunosuppressive doses of corticosteroids, the expected serum antibody response may not be obtained. However, immunization procedures may be undertaken in patients who are receiving corticosteroids as replacement therapy, e.g., for Addison’s disease.

Literature reports suggest an apparent association between use of corticosteroids and left ventricular free wall rupture after a recent myocardial infarction; therefore, therapy with corticosteroids should be used with great caution in these patients.

Usage in pregnancy: Since adequate human reproduction studies have not been done with corticosteroids, use of these drugs in pregnancy or in women of childbearing potential requires that the anticipated benefits be weighed against the possible hazards to the mother and embryo or fetus. Infants born of mothers who have received substantial doses of corticosteroids during pregnancy should be carefully observed for signs of hypoadrenalism.

Corticosteroids appear in breast milk and could suppress growth, interfere with endogenous corticosteroid production, or cause other unwanted effects. Mothers taking pharmacologic doses of corticosteroids should be advised not to nurse.

PRECAUTIONS:

General:

Following prolonged therapy, withdrawal of corticosteroids may result in symptoms of the corticosteroid withdrawal syndrome including fever, myalgia, arthralgia, and malaise. This may occur in patients even without evidence of adrenal insufficiency.

There is an enhanced effect of corticosteroids in patients with hypothyroidism and in those with cirrhosis.

Corticosteroids should be used cautiously in patients with ocular herpes simplex because of possible corneal perforation.

The lowest possible dose of corticosteroid should be used to control the condition under treatment, and when reduction in dosage is possible, the reduction should be gradual.

Psychic derangements may appear when corticosteroids are used, ranging from euphoria, insomnia, mood swings, personality changes, and severe depression, to frank psychotic manifestations. Also, existing emotional instability or psychotic tendencies may be aggravated by corticosteroids.

Aspirin should be used cautiously in conjunction with corticosteroids in hypoprothrombinemia.

Steroids should be used with caution in nonspecific ulcerative colitis, if there is a probability of impending perforation, abscess, or other pyogenic infection, diverticulitis, fresh intestinal anastomoses, active or latent peptic ulcer, renal insufficiency, hypertension, osteoporosis, and myasthenia gravis. Signs of peritoneal irritation following gastrointestinal perforation in patients receiving large doses of corticosteroids may be minimal or absent. Fat embolism has been reported as a possible complication of hypercortisonism.

When large doses are given, some authorities advise that corticosteroids be taken with meals and antacids taken between meals to help to prevent peptic ulcer.

Growth and development of infants and children on prolonged corticosteroid therapy should be carefully observed.

Steroids may increase or decrease motility and number of spermatozoa in some patients.

Phenytoin, phenobarbital, ephedrine, and rifampin may enhance the metabolic clearance of corticosteroids, resulting in decreased blood levels and lessened physiologic activity, thus requiring adjustment in corticosteroid dosage.

The prothrombin time should be checked frequently in patients who are receiving corticosteroids and coumarin anticoagulants at the same time because of reports that corticosteroids have altered the response to these anticoagulants. Studies have shown that the usual effect produced by adding corticosteroids is inhibition of response to coumarins, although there have been some conflicting reports of potentiation not substantiated by studies.

When corticosteroids are administered concomitantly with potassium-depleting diuretics, patients should be observed closely for development of hypokalemia.

Information for Patients:

Persons who are on immunosuppressant doses of corticosteroids should be warned to avoid exposure to chickenpox or measles. Patients should also be advised that if they are exposed, medical advice should be sought without delay.

ADVERSE REACTIONS:

Fluid and Electrolyte Disturbances

- Sodium retention
- Fluid retention
- Congestive heart failure in susceptible patients
- Potassium loss
- Hypokalemic alkalosis
- Hypertension

Musculoskeletal

- Muscle weakness
- Steroid myopathy
- Loss of muscle mass
- Osteoporosis
- Vertebral compression fractures
- Aseptic necrosis of femoral and humeral heads
- Pathologic fracture of long bones
- Tendon rupture

Gastrointestinal

- Peptic ulcer with possible perforation and hemorrhage
- Perforation of the small and large bowel, particularly in patients with inflammatory bowel disease
- Pancreatitis
- Abdominal distention
- Ulcerative esophagitis

Dermatologic

- Impaired wound healing
- Thin fragile skin
- Petechiae and ecchymoses
- Erythema
- Increased sweating
- May suppress reactions to skin tests
- Other cutaneous reactions, such as allergic dermatitis, urticaria, angioneurotic edema

Neurologic

- Convulsions
- Increased intracranial pressure with papilledema (pseudotumor cerbri) usually after treatment
- Vertigo
- Headache
- Psychic disturbances

Endocrine

- Menstrual irregularities
- Development of cushingoid state
- Suppression of growth in children
- Secondary adrenocortical and pituitary unresponsiveness, particularly in times of stress, as in trauma, surgery, or illness
- Decreased carbohydrate tolerance
- Manifestations of latent diabetes mellitus
- Increased requirements for insulin or oral hypoglycemic agents in diabetics
- Hirsutism

Ophthalmic

- Posterior subcapsular cataracts
- Increased intraocular pressure
- Glaucoma
- Exophthalmos

Metabolic

- Negative nitrogen balance due to protein catabolism

Other

- Hypersensitivity
- Thromboembolism
- Weight gain
- Increased appetite
- Nausea
- Malaise

To report SUSPECTED ADVERSE REACTIONS, contact Chartwell RX, LLC. Corp. at 1-845-232-1683, or FDA at 1-800-FDA-1088 or www.fda.gov/medwatch.

DOSAGE AND ADMINISTRATION:

For Oral Administration

DOSAGE REQUIREMENTS ARE VARIABLE AND MUST BE INDIVIDUALIZED ON THE BASIS OF THE DISEASE AND THE RESPONSE OF THE PATIENT.

The initial dosage varies from 25 to 300 mg a day depending on the disease being treated. In less severe diseases doses lower than 25 mg may suffice, while in severe diseases doses higher than 300 mg may be required. The initial dosage should be maintained or adjusted until the patient’s response is satisfactory. If satisfactory clinical response does not occur after a reasonable period of time, discontinue cortisone acetate tablets and transfer the patient to other therapy.

After a favorable initial response, the proper maintenance dosage should be determined by decreasing the initial dosage in small amounts to the lowest dosage that maintains an adequate clinical response.

Patients should be observed closely for signs that might require dosage adjustment, including changes in clinical status resulting from remissions or exacerbations of the disease, individual drug responsiveness, and the effect of stress (e.g., surgery, infection, trauma). During stress it may be necessary to increase dosage temporarily.

If the drug is to be stopped after more than a few days of treatment, it usually should be withdrawn gradually.

HOW SUPPLIED:

Cortisone Acetate Tablets, USP 25 mg: white to off-white, round scored tablets, debossed with “C” bisect “E” on one side and “113” on the other side.

Bottles of 30 tablets. NDC 62135-173-30

Store at 20° to 25°C (68° to 77°F) [See USP Controlled Room Temperature]. Protect from light and moisture.

Preserve in well closed containers, as defined in the USP.

Manufactured for:

Chartwell RX, LLC.

Congers, NY 10920

L71189

Revised 06/2024

PACKAGE LABEL.PRINCIPAL DISPLAY PANEL

Cortisone Acetate Tablets, USP 25 mg- NDC 62135-173-30- 30's Bottle of Label